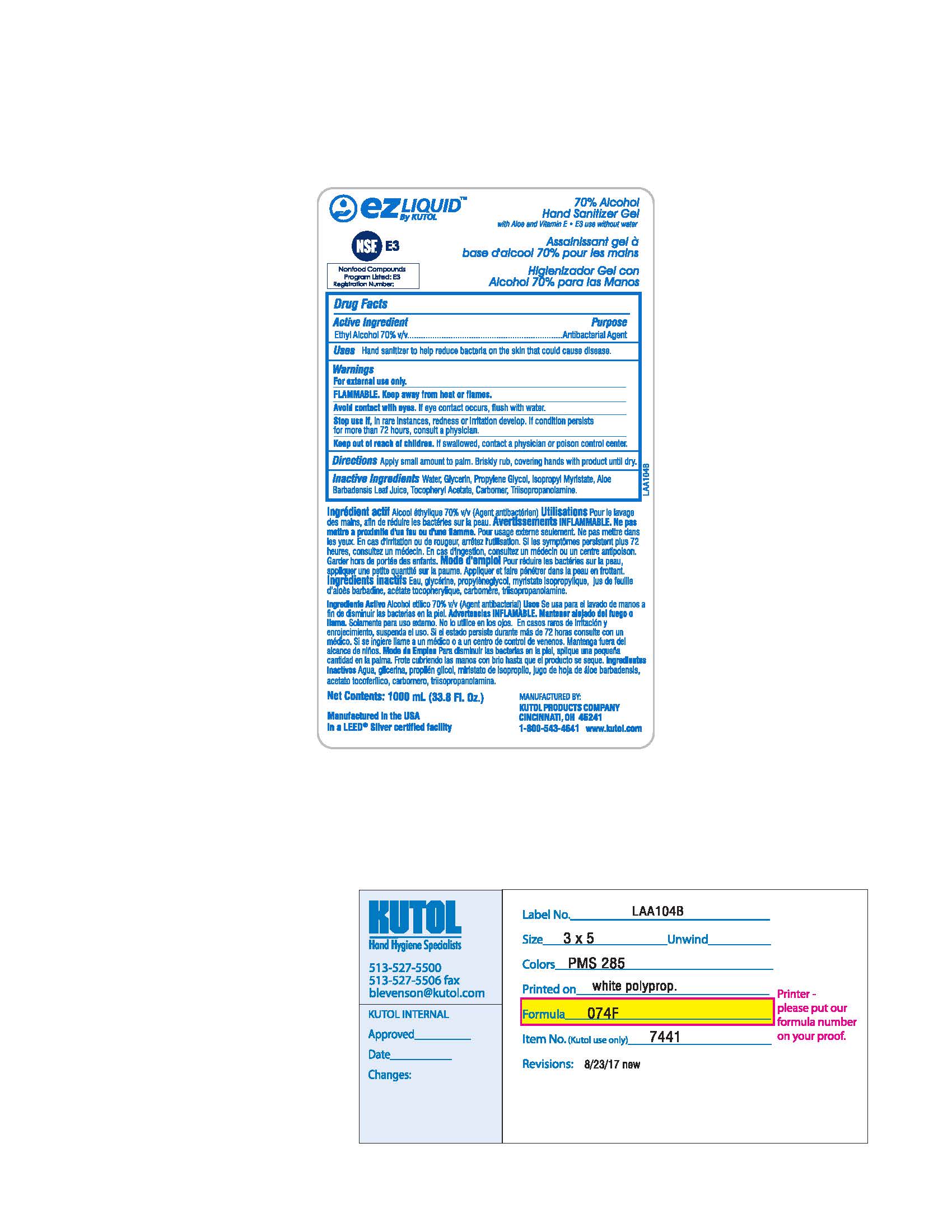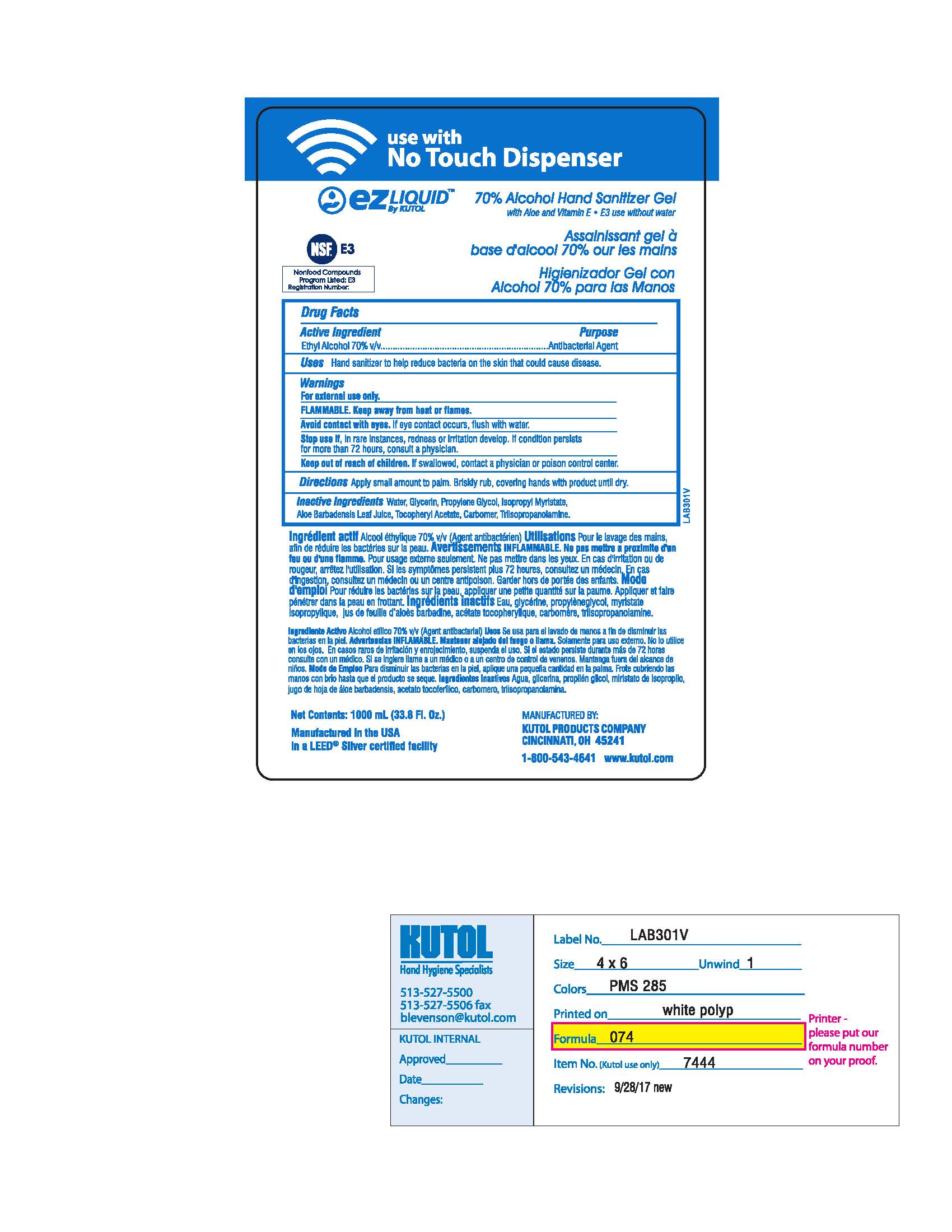 DRUG LABEL: 70% Alcohol Hand Sanitizer
NDC: 50865-074 | Form: SOAP
Manufacturer: Kutol Products Company, Inc.
Category: otc | Type: HUMAN OTC DRUG LABEL
Date: 20180226

ACTIVE INGREDIENTS: ALCOHOL 0.07 mg/1 mL
INACTIVE INGREDIENTS: CARBOXYPOLYMETHYLENE; .ALPHA.-TOCOPHEROL ACETATE, D-; TRIISOPROPANOLAMINE; ALOE VERA LEAF; PROPYLENE GLYCOL; ISOPROPYL MYRISTATE; GLYCERIN

70% Alcohol Hand Sanitizer Gel

ACTIVE INGREDIENT

Ethyl Alcohol 70% v/v.....Antibacterial Agent

INACTIVE INGREDIENT

Water, Glycerin, Propylene Glycol, Isopropyl Myristate, Aloe Barbadensis Leaf Juice, Tocopheryl Acetate, Carbomer, Triisopropanolamine

PURPOSE

For handwashing to help reduce bacteria on the skin

WARNINGS

For external use only.

Avoid contact with eyes. If eye contact occurs, flush eyes with water.

Stop use if, in rare instances, redness or irritation develop. If condition persists for more than 72 hours, consult a physician.

Keep out of reach of children. If swallowed, contact a physician or poison control center.

DOSAGE AND ADMINISTRATION

Apply to hair or body. Work into a rich lather. Massage hair and body completely for at least 30 seconds. Rinse thoroughly. Dry completely.

INDICATIONS AND USAGE

For handwashing to help reduce bacteria on the skin.

Avoid contact with eyes. If eye contact occurs, flush eyes with water.

Stop use if, in rare instances, redness or irritation develop. If condition persists for more than 72 hours, consult a physician.

Keep out of reach of children. If swallowed, contact a physician or poison control center.

Keep out of reach of children. If swallowed, contact a physician or poison control center.